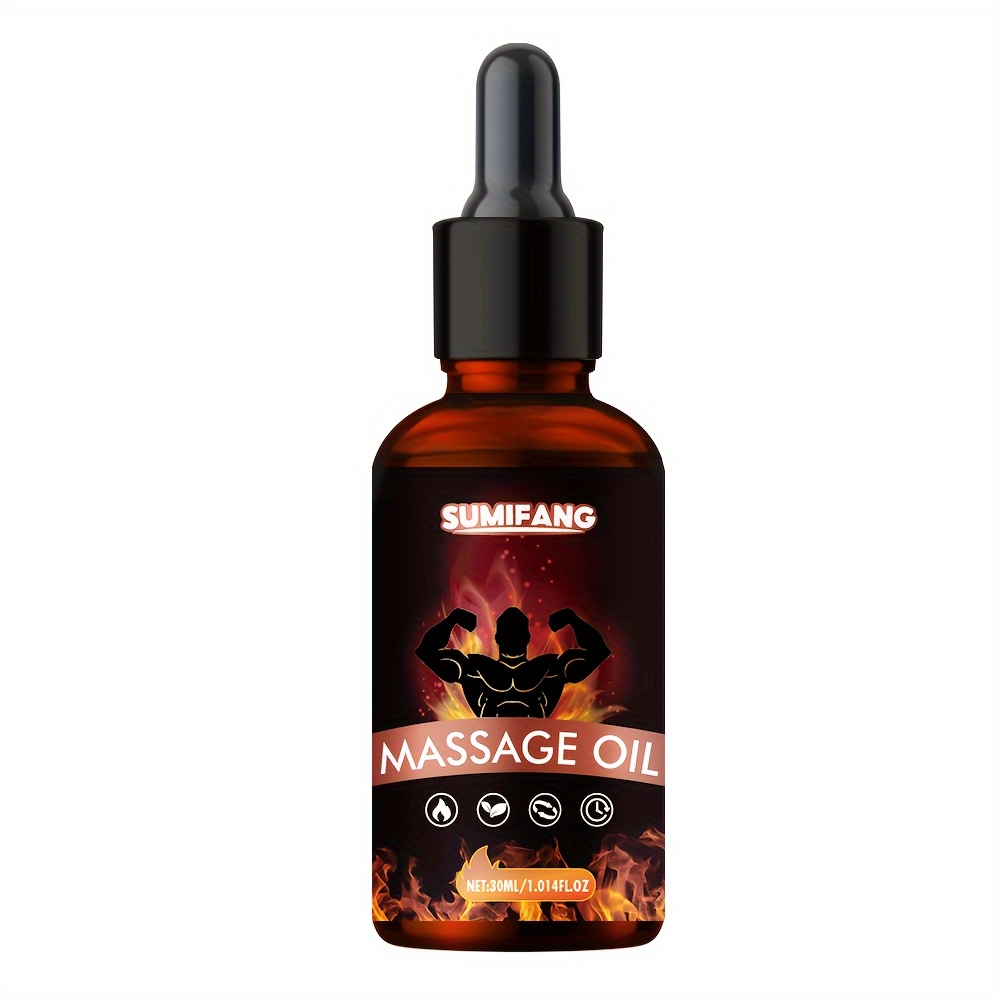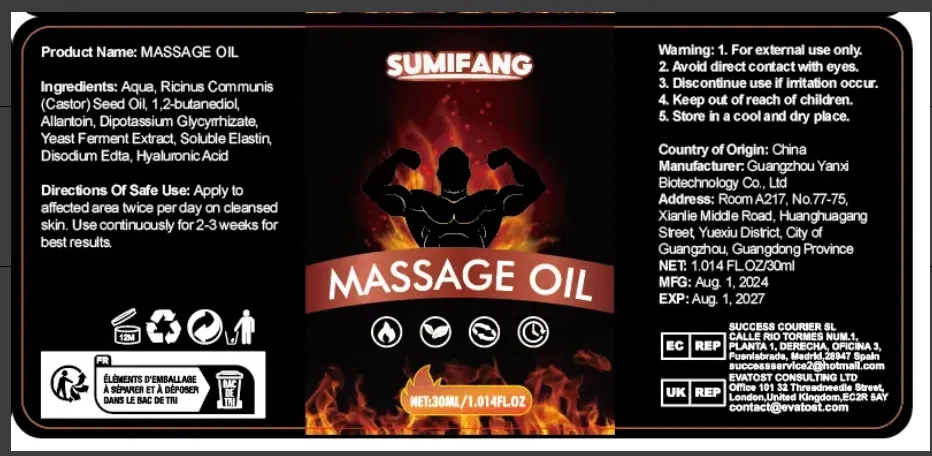 DRUG LABEL: Massage Oil
NDC: 84025-204 | Form: OIL
Manufacturer: Guangzhou Yanxi Biotechnology Co., Ltd
Category: otc | Type: HUMAN OTC DRUG LABEL
Date: 20241008

ACTIVE INGREDIENTS: CETEARYL OLIVATE 3 mg/100 mL; NIACINAMIDE 5 mg/100 mL
INACTIVE INGREDIENTS: WATER

DOSAGE AND ADMINISTRATION

Use for body massage

WARNINGS

Keep out of children

INACTIVE INGREDIENT

Aqua

INDICATIONS AND USAGE

for body care

keep out of children

PURPOSE

It relaxes and soothes the body